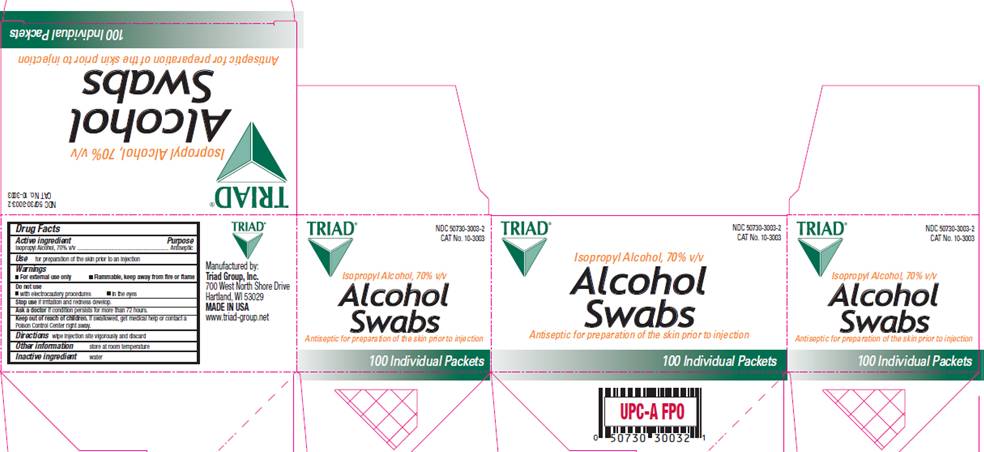 DRUG LABEL: Isopropyl alcohol
NDC: 50730-3003 | Form: SWAB
Manufacturer: H and P Industries, Inc. dba Triad Group
Category: otc | Type: HUMAN OTC DRUG LABEL
Date: 20091216

ACTIVE INGREDIENTS: Isopropyl alcohol .7 mL/1 1
INACTIVE INGREDIENTS: water

DRUG FACTS

ACTIVE INGREDIENT

Isopropyl Alcohol 70% v/v

PURPOSE

Antiseptic

USES

for preparation of the skin prior to injection

WARNINGS

- For external use only

- Flammable, keep away from fire or flame

Do not use

- with electrocautery procedures
- in the eyes

Stop use

if irritation and redness develop.

Ask a doctor

if condition persists for more than 72 hours.

KEEP OUT OF REACH OF CHILDREN

If swallowed, get medical help or contact a Poison Control Center right away.

DIRECTIONS

wipe injection site vigorously and discard.

OTHER INFORMATION

store at room temperature

INACTIVE INGREDIENT

water

PACKAGE INFORMATION

TRIAD
NDC 50730-3003-2
CAT No. 10-3003
70% Isopropyl Alcohol, v/v
Alcohol Swabs
Antiseptic for preparation of the skin prior to injection
100 Individual Packets
Manufactured by:
Triad Disposables, Inc.
700 West North Shore Drive
Hartland, WI 53029
MADE IN USA
www.triad-group.net